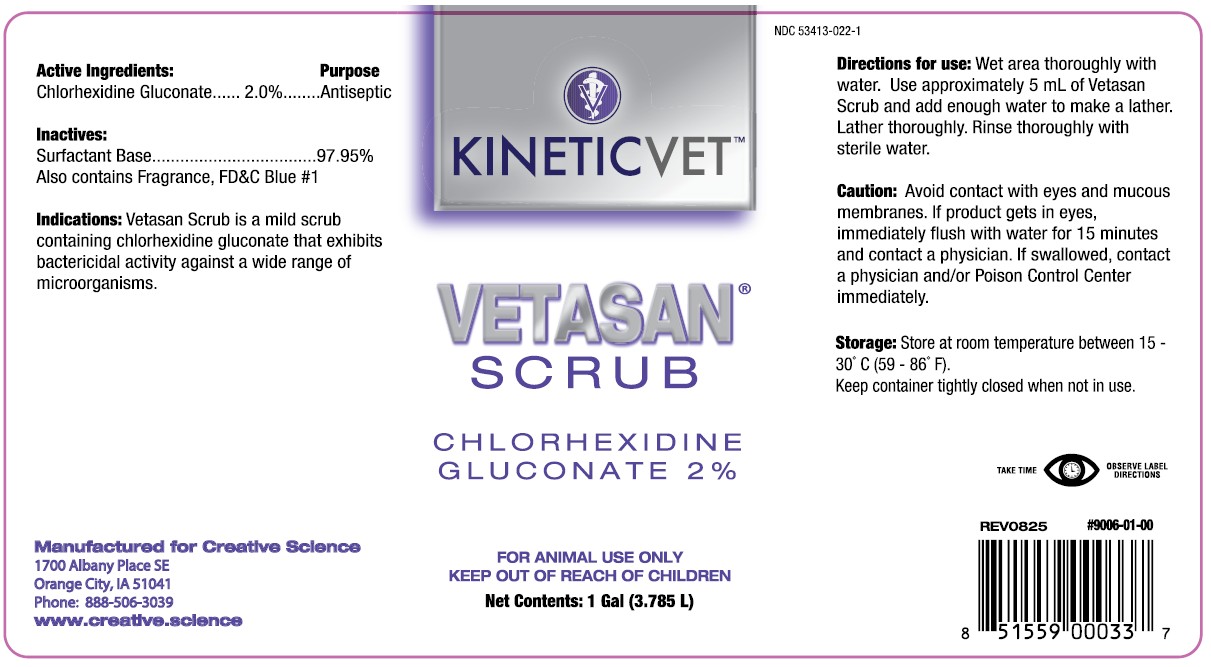 DRUG LABEL: VETASAN SCRUB
NDC: 53413-022 | Form: SOLUTION
Manufacturer: Creative Science
Category: animal | Type: OTC ANIMAL DRUG LABEL
Date: 20251231

ACTIVE INGREDIENTS: CHLORHEXIDINE GLUCONATE 2 g/0.1 L

VETASAN® SCRUB

Active Ingredients:

Chlorhexidine Gluconate........2.0%

Purpose

Antiseptic

Inactives:

Surfactant Base ............... 97.95%

Also contains Fragrance, FD&C Blue #1

Indications:

Vetasan Scrub is a mild scrub containing chlorhexidine gluconate that exhibits bactericidal activity against a wide range of microorganisms.

Manufactured for Creative Science

1700 Albany Place SE

Orange City, IA 51041

Phone: 888-506-3039

www.creative.science

NDC 53413-022-11

Directions for use:

Wet area thoroughly with water. Use approximately 5 ml of Vetasan Scrub and add enough water to make a lather. Lather thoroughly. Rinse thoroughly with sterile water.

Caution:

Avoid contact with eyes and mucous membranes. If product gets in eyes, immediately flush with water for 15 minnutes and contact a physician. If swallowed, contact a physician and/or Poison Control Center immediately.

Storage:

Store at room temperature between 15 - 30°C (59 - 86°F).

Keep container tightly closed when not in use.

TAKE TIME OBSERVE LABEL INSTRUCTIONS

REV0825 #9006-01-00

UPC 851559000337

KEEP OUT OF REACH OF CHILDREN

FOR ANIMAL USE ONLY
KEEP OUT OF REACH OF CHILDREN

PACKAGE LABEL

VETASAN® SCRUB

CHLORHEXIDINE GLUCONATE 2%

FOR ANIMAL USE ONLY

KEEP OUT OF REACH OF CHILDREN

Net Contents: 1 Gal (3.785 L)